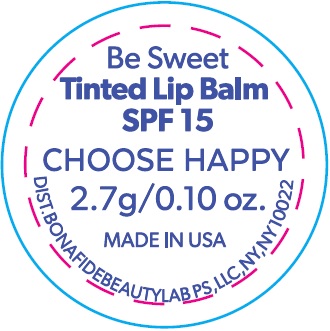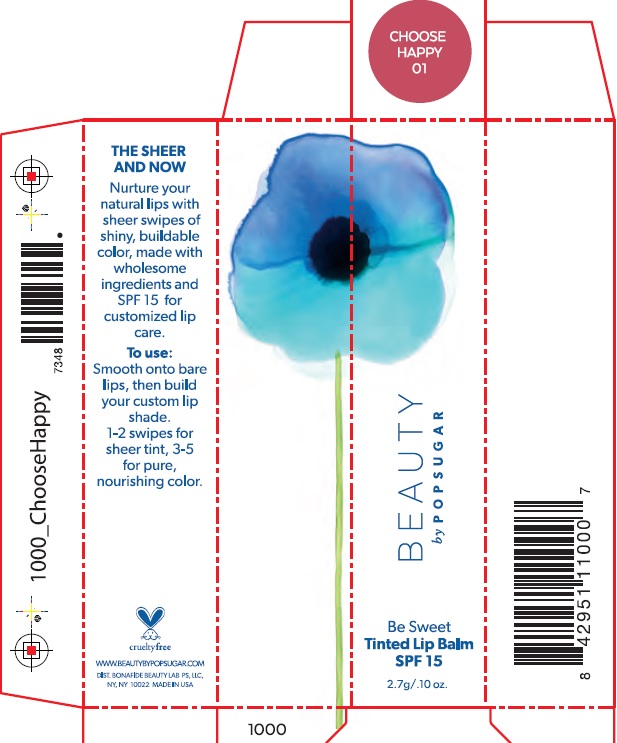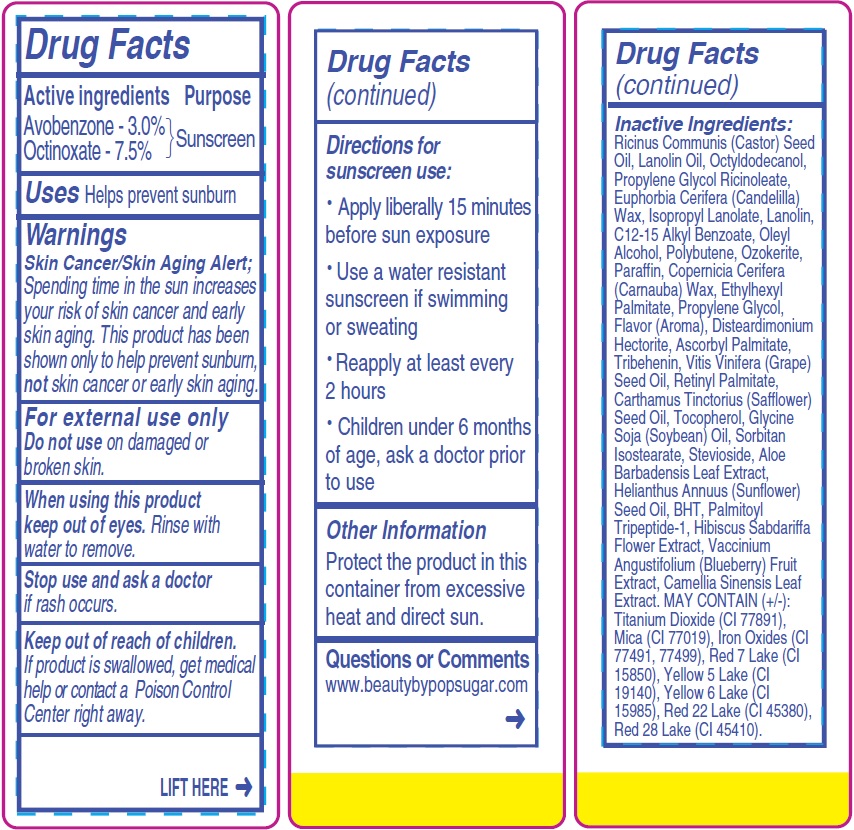 DRUG LABEL: Be Sweet SPF 15 Tinted
NDC: 72112-001 | Form: GEL
Manufacturer: Bona Fide Beauty Lab PS LLC
Category: otc | Type: HUMAN OTC DRUG LABEL
Date: 20180216

ACTIVE INGREDIENTS: AVOBENZONE 30 mg/1 g; OCTINOXATE 75 mg/1 g
INACTIVE INGREDIENTS: CASTOR OIL; LANOLIN OIL; OCTYLDODECANOL; PROPYLENE GLYCOL RICINOLEATE; CANDELILLA WAX; LANOLIN; ALKYL (C12-15) BENZOATE; OLEYL ALCOHOL; POLYBUTENE (1400 MW); CERESIN; PARAFFIN; CARNAUBA WAX; ETHYLHEXYL PALMITATE; PROPYLENE GLYCOL; METHYL SALICYLATE; DISTEARDIMONIUM HECTORITE; ASCORBYL PALMITATE; TRIBEHENIN; GRAPE SEED OIL; VITAMIN A PALMITATE; SAFFLOWER OIL; TOCOPHEROL; SOYBEAN OIL; SORBITAN ISOSTEARATE; STEVIOSIDE; ALOE VERA LEAF; SUNFLOWER OIL; BUTYLATED HYDROXYTOLUENE; PALMITOYL TRIPEPTIDE-1; HIBISCUS SABDARIFFA FLOWER; LOWBUSH BLUEBERRY; GREEN TEA LEAF

Be Sweet SPF 15 Tinted Lip Balm Choose Happy

Active ingredients

Avobenzone - 3.0%
Octinoxate - 7.5%

Purpose

Sunscreen

Uses

Helps prevent sunburn

Warnings

Skin Cancer/Skin Aging Alert; Spending time in the sun increases your risk of skin cancer and early skin aging. This product has been shown only to help prevent sunburn, not skin cancer or early skin aging.

For external use only

Do not use

on damaged or broken skin.

When using this product

keep out of eyes. Rinse with water to remove.

Stop use and ask a doctor

if rash occurs.

Keep out of reach of children.

If product is swallowed, get medical help or contact a Poison Control Center right away.

Directions for sunscreen use:

- Apply liberally 15 minutes before sun exposure
- Use a water resistant sunscreen if swimming or sweating
- Reapply at least every 2 hours
- Children under 6 months of age, ask a doctor prior to use

Other Information

Protect the product in this container from excessive heat and direct sun.

Questions or Comments

www.beautybypopsugar.com

Inactive Ingredients:

Ricinus Communis (Castor) Seed Oil, Lanolin Oil, Octyldodecanol, Propylene Glycol Ricinoleate, Euphorbia Cerifera (Candelilla) Wax, Isopropyl Lanolate, Lanolin, C12-15 Alkyl Benzoate, Oleyl Alcohol, Polybutene, Ozokerite, Paraffin, Copernicia Cerifera (Carnauba) Wax, Ethylhexyl Palmitate, Propylene Glycol, Flavor (Aroma), Disteardimonium Hectorite, Ascorbyl Palmitate, Tribehenin, Vitis Vinifera (Grape) Seed Oil, Retinyl Palmitate, Carthamus Tinctorius (Safflower) Seed Oil, Tocopherol, Glycine Soja (Soybean) Oil, Sorbitan Isostearate, Stevioside, Aloe Barbadensis Leaf Extract, Helianthus Annuus (Sunflower) Seed Oil, BHT, Palmitoyl Tripeptide-1, Hibiscus Sabdariffa Flower Extract, Vaccinium Angustifolium (Blueberry) Fruit Extract, Camellia Sinensis Leaf Extract. MAY CONTAIN (+/-): Titanium Dioxide (CI 77891), Mica (CI 77019), Iron Oxides (CI
77491, 77499), Red 7 Lake (CI 15850), Yellow 5 Lake (CI 19140), Yellow 6 Lake (CI 15985), Red 22 Lake (CI 45380), Red 28 Lake (CI 45410).